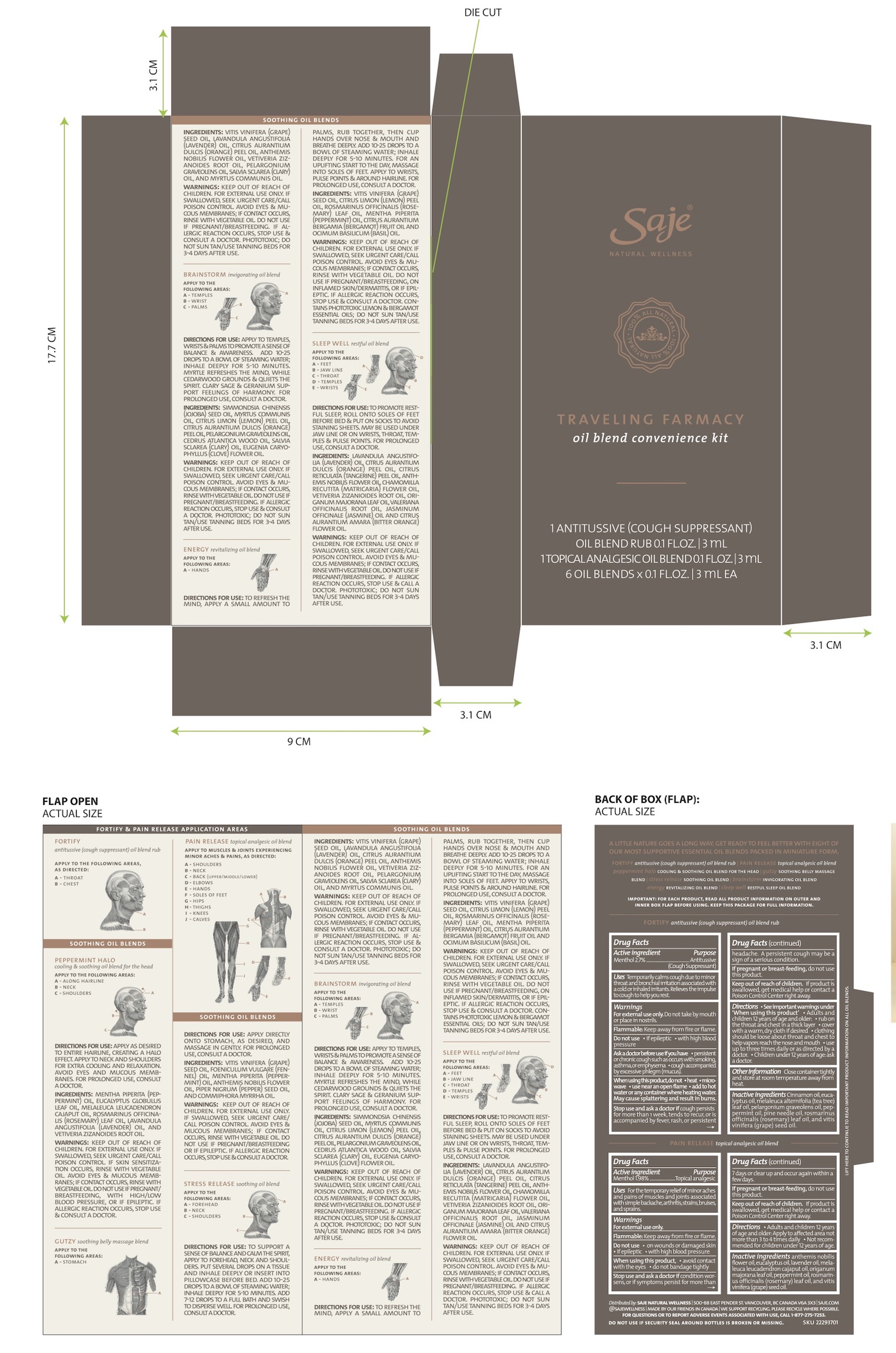 DRUG LABEL: Traveling Farmacy
NDC: 70983-020 | Form: KIT | Route: TOPICAL
Manufacturer: Saje Natural Business Inc.
Category: otc | Type: HUMAN OTC DRUG LABEL
Date: 20260113

ACTIVE INGREDIENTS: MENTHOL 24.03 mg/1 mL; MENTHOL 17.62 mg/1 mL
INACTIVE INGREDIENTS: CINNAMON OIL; PELARGONIUM GRAVEOLENS FLOWER OIL; ROSEMARY OIL; GRAPE SEED OIL; EUCALYPTUS OIL; PINE NEEDLE OIL (PINUS SYLVESTRIS); TEA TREE OIL; PEPPERMINT OIL; PEPPERMINT OIL; ROSEMARY OIL; SWEET MARJORAM OIL; EUCALYPTUS OIL; CAJUPUT OIL; GRAPE SEED OIL; LAVENDER OIL; CHAMAEMELUM NOBILE FLOWER OIL

Traveling Farmacy

Fortify

Purpose: Antitussive (Cough Suppressant)

Fortify

Adults and children 12 years and older: rub on the throat and chest in a thick layer. Cover with a warm, dry cloth if desired. Clothing should be loose about throat and chest to help vapors reach the nose and mouth. Use up to three times daily or as directed by a doctor. Children under 12 years of age: ask a doctor.

Apply to the following areas, as directed: A - throat; B – chest.

IMPORTANT: READ ALL PRODUCT INFORMATION BEFORE USING. KEEP THIS PACKAGE FOR FULL INFORMATION.

Fortify

Uses: Temporarily calms cough due to minor throat and bronchial irritation associated with a cold or inhaled irritants. Relieves the impulse to cough to help you rest.

Fortify

Active ingredients: Menthol 2.7% ;

Purpose: Antitussive (cough suppresant)

Fortify

For external use only. Do not take by mouth or place in nostrils. Flammable: Keep away from fire or flame. Do not use • if epileptic • with high blood pressure. Ask a doctor before use if you have • persistent or chronic cough such as occurs with smoking, asthma, or emphysema • cough accompanied by excessive phlegm (mucus). When using this product, do not • heat • microwave • use near an open flame • add to hot water or any container where heating water. May cause splattering and result in burns. Stop use and ask a doctor if cough persists for more than 1 week, tends to recur, or is accompanied by fever, rash, or persistent headache. A persistent cough may be a sign of a serious condition. If pregnant or breast-feeding, do not use this product.

Fortify

Keep out of reach of children. If product is swallowed, get medical help or contact a Poison Control Center right away.

Fortify

inactive ingredients: cinnamon oil, eucalyptus oil, melaleuca alternifolia (tea tree) leaf oil, pelargonium graveolens oil, peppermint oil, pine needle oil, rosmarinus officinalis (rosemary) leaf oil, and vitis vinifera (grape) seed oil.

Pain Release

Purpose: Topical analgesic

Pain Release

Adults and children 12 years of age and older: Apply to affected area not more than 3 to 4 times daily. Not recommended for children under 12 years of age.

Apply to muscles & joints experiencing minor aches & pains, as directed: A - shoulders B - neck C - back

IMPORTANT: READ ALL PRODUCT INFORMATION BEFORE USING. KEEP THIS PACKAGE FOR FULL INFORMATION.

Pain Release

For the temporary relief of minor aches and pains of muscles and joints associated with simple backache, arthritis, strains, bruises, and sprains.

Pain Release

Active ingredient: Menthol 1.98%

Purpose: Topical analgesic

Fortify

Other information: Close container tightly and store at room temperature away from heat.

Pain Release

For external use only. Flammable. Keep away from fire or flame. Do not use • on wounds or damaged skin • if epileptic • with high blood pressure. When using this product • avoid contact with the eyes • do not bandage tightly. Stop use and ask a doctor if condition worsens, or if symptoms persist for more than 7 days or clear up and occur again within a few days. If pregnant or breast-feeding, do not use this product.

Pain Release

Keep out of reach of children. If product is swallowed, get medical help or contact a Poison Control Center right away.

Pain Release

anthemis nobilis flower oil, eucalyptus oil, lavender oil, melaleuca leucadendron cajaput oil, origanum majorana leaf oil, peppermint oil, rosmarinus officinalis (rosemary) leaf oil, and vitis vinifera (grape) seed oil.

Peppermint halo

Directions for use: apply as desired to entire hairline, creating a halo effect. apply to neck and shoulders for extra cooling and relaxation. avoid eyes and mucous membranes. for prolonged use, consult a doctor.

Apply to the following areas: A- Along hairline; B- Neck; C- Shoulders

Peppermint Halo

Ingredients: mentha piperita (peppermint) oil, eucalyptus globulus leaf oil, melaleuca leucadendron cajaput oil, rosmarinus officinalis (rosemary) leaf oil, lavandula angustifolia (lavender) oil, and vetiveria zizanoides root oil.

Peppermint Halo

Warnings: - keep out of reach of children. - for external use only. if swallowed, seek urgent care/call poison control. - if skin sensitization occurs, rinse with vegetable oil. - avoid eyes & mucous membranes; if contact occurs, rinse with vegetable oil. - do not use if pregnant/breastfeeding, with high/low blood pressure, or if epileptic. - if allergic reaction occurs, stop use & consult a doctor.

Gutzy

Directions for use: apply directly onto stomach, as desired, and massage in gently. for prolonged use, consult a doctor.

Apply to the following areas: A- Stomach

Gutzy

Ingredients: vitis vinifera (grape) seed oil, foeniculum vulgare (fennel) oil, mentha piperita (peppermint) oil, anthemis nobilis flower oil, piper nigrum (pepper) seed oil, and commiphora myrrha oil.

Gutzy

- keep out of reach of children. - for external use only. if swallowed, seek urgent care/call poison control. - avoid eyes & mucous membranes; if contact occurs, rinse with vegetable oil. - do not use if pregnant/breastfeeding or if epileptic. - if allergic reaction occurs, stop use & consult a doctor.

Stress Release

Directions for use: to support a sense of balance and calm the spirit, apply to forehead, neck and shoulders. put several drops on a tissue & inhale deeply or insert into pillowcase before bed. add 10-25 drops to a bowl of steaming water; inhale deeply for 5-10 minutes. add 7-12 drops to a full bath & swish to disperse well. for prolonged use, consult a doctor.

Apply to the following areas: A- Forehead; B- Neck; C-Shoulders

Stress Release

Ingredients: vitis vinifera (grape) seed oil, lavandula angustifolia (lavender) oil, citrus aurantium dulcis (orange) peel oil, anthemis nobilis flower oil, vetiveria zizanoides root oil, pelargonium graveolens oil, salvia sclarea (clary) oil, and myrtus communis oil.

Stress Release

- keep out of reach of children. - for external use only. if swallowed, seek urgent care/call poison control. - avoid eyes & mucous membranes; if contact occurs, rinse with vegetable oil. - do not use if pregnant/breastfeeding. - if allergic reaction occurs, stop use & consult a doctor. – phototoxic; do not sun tan/use tanning beds for 3-4 days after use.

Brainstorm

Directions for use: apply to temples, wrists & palms to promote a sense of balance & awareness. add 10-25 drops to a bowl of steaming water; inhale deeply for 5-10 minutes. myrtle refreshes the mind, while cedarwood grounds & quiets the spirit. clary sage & geranium support feelings of harmony. for prolonged use, consult a doctor.

Apply to the following areas: A- Temples; B- Wrists; C- Palms

Brainstorm

Ingredients: simmondsia chinensis (jojoba) seed oil, myrtus communis oil, citrus limon (lemon) peel oil, citrus aurantium dulcis (orange) peel oil, pelargonium graveolens oil, cedrus atlantica wood oil, salvia sclarea (clary) oil, eugenia caryophyllus (clove) flower oil.

Energy

Directions for use: to refresh the mind, apply a small amount to palms, rub together, then cup hands over nose & mouth & breathe deeply. add 10-25 drops to a bowl of steaming water; inhale deeply for 5-10 minutes. for an uplifting start to the day, massage into soles of feet. apply to wrists, pulse points & around hairline. for prolonged use, consult a doctor.

Apply to the following areas: A- Hands

Energy

Ingredients: vitis vinifera (grape) seed oil, citrus limon (lemon) peel oil, rosmarinus officinalis (rosemary) leaf oil, mentha piperita (peppermint) oil, citrus aurantium bergamia (bergamot) fruit oil and ocimum basilicum (basil) oil.

Brainstorm

- keep out of reach of children. - for external use only. if swallowed, seek urgent care/call poison control. - avoid eyes & mucous membranes; if contact occurs, rinse with vegetable oil. - do not use if pregnant/breastfeeding. - if allergic reaction occurs, stop use & consult a doctor. - phototoxic; do not sun tan/use tanning beds for 3-4 days after use.

Sleep Well

Directions for use: to promote restful sleep, roll onto soles of feet before bed & put on socks to avoid staining sheets. may be used under jaw line or on wrists, throat, temples & pulse points. for prolonged use, consult a doctor.

Apply to the following areas; A- Feet; B- Jawline; C- Throat; D- Temples; E- Wrists

Sleep Well

ingredients: lavandula angustifolia (lavender) oil, citrus aurantium dulcis (orange) peel oil, citrus reticulata (tangerine) peel oil, anthemis nobilis flower oil, chamomilla recutita (matricaria) flower oil, vetiveria zizanioides root oil, origanum majorana leaf oil, valeriana officinalis root oil, jasminum officinale (jasmine) oil and citrus aurantium amara (bitter orange) flower oil.

Energy

- keep out of reach of children. - for external use only. if swallowed, seek urgent care/call poison control. - avoid eyes & mucous membranes; if contact occurs, rinse with vegetable oil. - do not use if pregnant/breastfeeding, on inflamed skin/dermatitis, or if epileptic. - if allergic reaction occurs, stop use & consult a doctor. - contains phototoxic lemon & bergamot essential oils; do not sun tan/use tanning beds for 3-4 days after use.

Sleep Well

- keep out of reach of children. - for external use only. if swallowed, seek urgent care/call poison control. - avoid eyes & mucous membranes; if contact occurs, rinse with vegetable oil. - do not use if pregnant/breastfeeding. - if allergic reaction occurs, stop use & call a doctor. - phototoxic; do not sun tan/use tanning beds for 3-4 days after use.

Traveling Farmacy

Oil Blend Convenience Kit

1 antitussive (cough suppressant) oil blend rub, 0.1 fl. oz. (3 ml); 1 topical analgesic oil blend, 0.1 fl. oz. (3 ml); 6 oil blends, 0.1 fl. oz. (3 ml) ea

Traveling Farmacy

Fortify Oil Blend; Pain Release Oil Blend; Peppermint Halo Oil Blend; Gutzy Oil Blend; Stress Release Oil Blend; Brainstorm Oil Blend; Energy Oil Blend; Sleep Well Oil Blend.

Traveling Farmacy - Company information and other information

Distributed by: saje natural wellness 500 - 88 east pender st. vancouver, bc canada v6a 3x3; saje.com; @SAJEWELLNESS; Made by our friends in Canada.

FOR QUESTIONS OR TO REPORT ADVERSE EVENTS ASSOCIATED WITH USE, CALL 1-877-275-7253

DO NOT USE IF SECURITY SEAL AROUND BOTTLES IS BROKEN OR MISSING